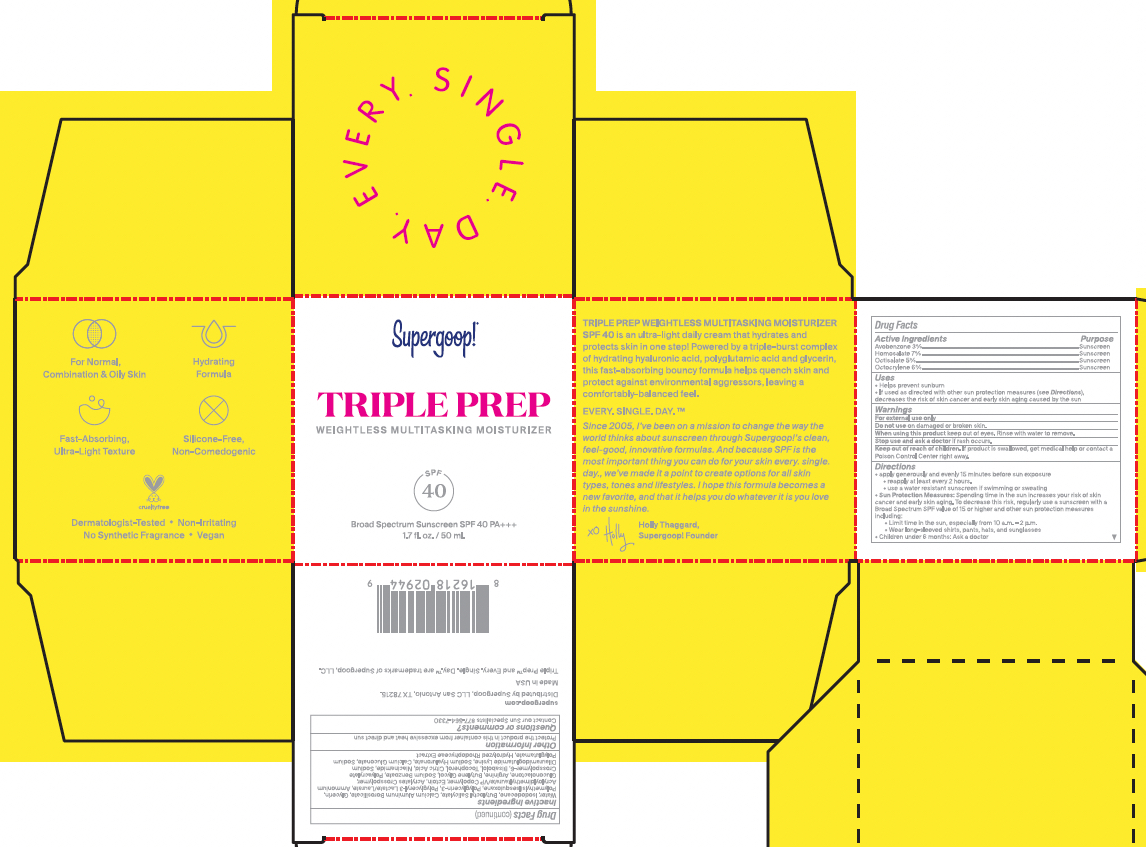 DRUG LABEL: Triple Prep SPF 40
NDC: 75936-621 | Form: LOTION
Manufacturer: Supergoop, LLC
Category: otc | Type: HUMAN OTC DRUG LABEL
Date: 20241205

ACTIVE INGREDIENTS: OCTISALATE 5 g/100 mL; AVOBENZONE 3 g/100 mL; OCTOCRYLENE 6 g/100 mL; HOMOSALATE 7 g/100 mL
INACTIVE INGREDIENTS: SODIUM BENZOATE; CITRIC ACID MONOHYDRATE; ARGININE; SODIUM DILAURAMIDOGLUTAMIDE LYSINE; POLYMETHYLSILSESQUIOXANE (11 MICRONS); AMMONIUM ACRYLOYLDIMETHYLTAURATE/VP COPOLYMER; TOCOPHEROL; ECTOINE; LEVOMENOL; CALCIUM SODIUM PHOSPHATE; GLYCERIN; POLYGLYCERIN-3; POLYGLYCERYL-3 LAURATE; HYALURONATE SODIUM; SODIUM LAUROYL GLUTAMATE; ACRYLATES CROSSPOLYMER-4; GLUCONOLACTONE; NIACINAMIDE; AMMONIUM ACRYLOYLDIMETHYLTAURATE, DIMETHYLACRYLAMIDE, LAURYL METHACRYLATE AND LAURETH-4 METHACRYLATE COPOLYMER, TRIMETHYLOLPROPANE TRIACRYLATE CROSSLINKED (45000 MPA.S); BUTYLENE GLYCOL; CALCIUM GLUCONATE; WATER; ISODODECANE; BUTYLOCTYL SALICYLATE

Triple Prep Weightless multitasking moisturizer SPF 40

ACTIVE INGREDIENT

Active Ingredients: Avobenzone 3%, Homosalate 7%, Octisalate 5%, Octocrylene 6%

PURPOSE

Helps prevent sunburn

If used as directed with other sun protection measures (see Directions), decreases the risk of skin cancer and early skin aging caused by the sun

Keep out of reach of children. If product is swallowed, get medical help, or contact a poison control center right away.

WARNINGS

For External use only

Do not use on damaged or broken skin

When using this product, keep out of eyes. Rinse with water to remove

Stop use and ask a doctor if rash occurs

DOSAGE AND ADMINISTRATION

Apply generously and evenly 15 minutes before sun exposure

Reapply at least every 2 hours

Use a water-resistant sunscreen if swimming or sweating

Sun Protection Measures: Spending time in the sun increases your risk of skin cancer and early skin aging. To decrease this risk, regularly use a sunscreen with a Broad Spectrum SPF value of 15 or higher and other sun protection measures including:

Limit time in the sun, especially from 10 a.m.- 2 p.m.

Wear long-sleeved shirts, pants, hats, and sunglasses

Children under 6 months: Ask a doctor

INACTIVE INGREDIENT

Inactive Ingredients: Water, Isododecane, Butyloctyl Salicylate, Calcium Aluminum Borosilicate, Glycerin, Polymethylsilsesquioxane, Polyglycerin-3, Polyglyceryl-3 Lactate/Laurate, Ammonium Acryloyldimethyltaurate/VP Copolymer, Ectoin, Acrylates Crosspolymer, Gluconolactone, Arginine, Butylene Glycol, Sodium Benzoate, Polyacrylate Crosspolymer-6, Bisabolol, Tocopherol, Citric Acid, Niacinamide, Sodium Dilauramidoglutamide Lysine, Sodium Hyaluronate, Calcium Gluconate, Sodium Polyglutamate, Hydrolyzed Rhodophyceae Extract

PACKAGE LABEL

TRIPLE PREP

Weightless Multitasking Moisturizer

SPF 40

Broad Spectrum Sunscreen SPF 40 PA +++

1.7 fl. oz. / 50 mL